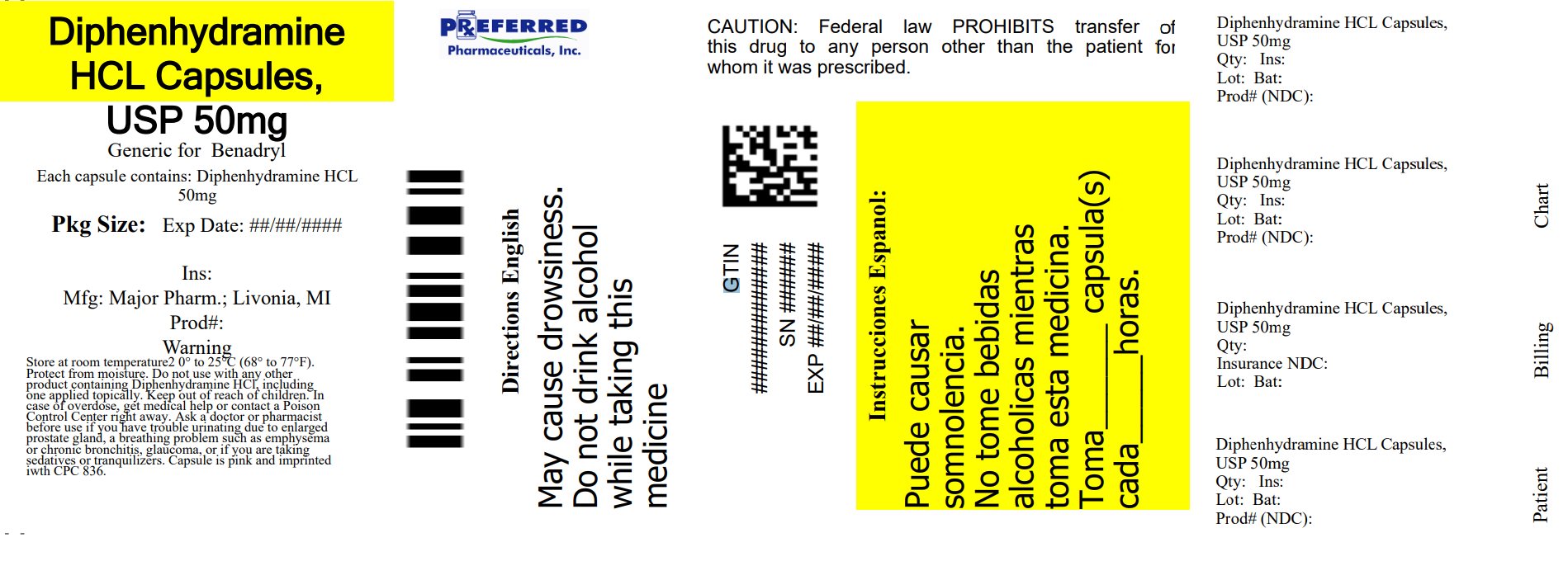 DRUG LABEL: Banophen
NDC: 68788-7830 | Form: CAPSULE
Manufacturer: Preferred Pharmaceuticals Inc.
Category: otc | Type: HUMAN OTC DRUG LABEL
Date: 20250328

ACTIVE INGREDIENTS: DIPHENHYDRAMINE HYDROCHLORIDE 50 mg/1 1
INACTIVE INGREDIENTS: D&C RED NO. 28; FD&C BLUE NO. 1; FD&C RED NO. 40; GELATIN, UNSPECIFIED; LACTOSE MONOHYDRATE; STARCH, CORN

0836-Major(100C/1000C)

Active Ingredient (in each banded capsule)

Diphenhydramine Hydrochloride 50 mg

Purpose

Antihistamine

Use

Temporarily relieves these symptoms due to hay fever or other upper respiratory allergies

- runny nose
- sneezing
- itchy, watery eyes
- itchy throat and nose
- Temporarily relieves these symptoms due to the common cold
  - runny nose
  - sneezing

WARNINGS

Do not use

- to make a child sleepy
- with any other product containing diphenhydramine, even one used on skin

Ask a doctor before use if you have

- glaucoma
- a breathing problem such as emphysema or chronic bronchitis
- trouble urinating due to an enlarged prostate gland

Ask a doctor or pharmacist

before use if you are taking sedatives or tranquilizers

When using this product

- marked drowsiness may occur
- avoid alcoholic drinks
- alcohol, sedatives, and tranquilizers may increase drowsiness
- be careful when driving a motor vehicle or operating machinery
- excitability may occur, especially in children

If pregnant or breast-feeding

ask a health professional before use.

KEEP OUT OF REACH OF CHILDREN

In case of overdose, get medical help or contact a Poison Control Center right away.

Directions

- Take every 4-6 hours
- Do not take more than 6 doses in 24 hours

adults and children 12 years of age and over | Take 1 capsule (50 mg)
children under 12 years of age | ask a doctor, the proper dosage strength is not available in this package**
**Do not attempt to break capsules. The proper dosage strength and dosing information for children under 12 years of age is available on the 25 mg package.

Other Information

- Store at room temperature, USP.
- Do not use if either capsule band or imprinted safety seal under cap is broken or missing
- Protect from moisture
- Contains lactose

Inactive Ingredients

D&C Red #28, FD&C Blue #1, FD&C Red #40, Gelatin, Lactose and Starch.

Questions?

Questions or comments? (800) 616-2471

Distributed by

MAJOR® PHARMACEUTICALS
17177 N Laurel Park Drive, Suite 233,
Livonia, MI 48152

Repackaged By: Preferred Pharmaceuticals Inc.

NDC 68788-7830